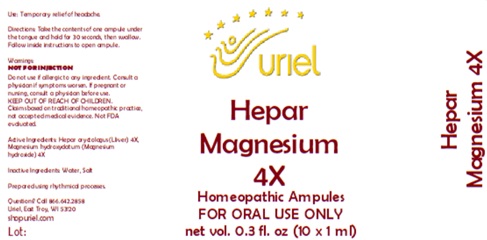 DRUG LABEL: Hepar Magnesium 4
NDC: 48951-5041 | Form: LIQUID
Manufacturer: Uriel Pharmacy Inc.
Category: homeopathic | Type: HUMAN OTC DRUG LABEL
Date: 20251126

ACTIVE INGREDIENTS: MAMMAL LIVER 4 [hp_X]/1 mL; MAGNESIUM HYDROXIDE 4 [hp_X]/1 mL
INACTIVE INGREDIENTS: WATER; SODIUM CHLORIDE

Hepar Magnesium 4

PURPOSE

Use: Temporary relief of headache.

INDICATIONS AND USAGE

FOR ORAL USE ONLY

DOSAGE AND ADMINISTRATION

Directions: Take the contents of one ampule under the tongue and hold for 30 seconds, then swallow. Follow inside instructions to open ampule.

KEEP OUT OF REACH OF CHILDREN.

Warnings:
NOT FOR INJECTION
Do not use if allergic to any ingredient. Consult a physician if symptoms worsen. If pregnant or nursing, consult a physician before use.
Claims based on traditional homeopathic practice, not accepted medical evidence. Not FDA evaluated.

Active Ingredients: Hepar oryctolagus (Lliver) 4X,
Magnesium hydroxydatum (Magnesium hydroxide) 4X

Inactive Ingredients: Water, Salt

Questions? Call 866.642.2858
Uriel, East Troy, WI 53120
shopuriel.com

Lot: